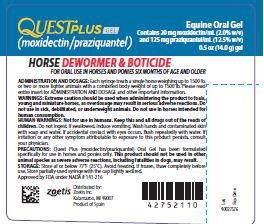 DRUG LABEL: Quest Plus
NDC: 54771-7521 | Form: GEL
Manufacturer: Zoetis Inc.
Category: animal | Type: OTC ANIMAL DRUG LABEL
Date: 20210105

ACTIVE INGREDIENTS: MOXIDECTIN 19.5 mg/1 g; PRAZIQUANTEL 121.7 mg/1 g

QUEST® PLUS GEL
(moxidectin/praziquantel)

Equine Oral Gel

Contains 20 mg moxidectin/mL (2.0% w/v)
and 125 mg praziquantel/mL (12.5% w/v)

DEWORMER & BOTICIDE

FOR ORAL USE IN HORSES AND PONIES
SIX MONTHS OF AGE AND OLDER

INDICATIONS

QUEST PLUS Gel (moxidectin/praziquantel) when administered at the recommended dose level of 0.4 mg moxidectin/kg and 2.5 mg praziquantel/kg (2.2 lb) body weight is effective in the treatment and control of the following stages of gastrointestinal parasites in horses and ponies:

Large Strongyles:

Strongylus vulgaris – (adults and L4/L5 arterial stages)

Strongylus edentatus – (adults and tissue stages)

Triodontophorus brevicauda – (adults)

Triodontophorus serratus – (adults)

Small Strongyles(adults):

Cyathostomumspp., including

Cyathostomum catinatum

Cyathostomum pateratum

Cylicostephanus spp., including

Cylicostephanuscalicatus

Cylicostephanus goldi

Cylicostephanus longibursatus

Cylicostephanus minutus

Cylicocyclus spp., including

Cylicocyclus insigne

Cylicocyclus leptostomum

Cylicocyclus nassatus

Cylicocyclus radiatus

Coronocyclusspp., including

Coronocyclus coronatus

Coronocyclus labiatus

Coronocyclus labratus

Gyalocephalus capitatus

Petrovinema poculatus

Small Strongyles:

Undifferentiated lumenal larvae

Encysted cyathostomes:

Late L3 and L4 mucosal cyathostome larvae

Ascarids:

Parascarisequorum – (adults and L4 larval stages)

Pinworms:

Oxyuris equi – (adults and L4 larval stages)

Hairworms:

Trichostrongylus axei– (adults)

Large-mouth stomach worms:

Habronema muscae– (adults)

Horse stomach bots:

Gasterophilus intestinalis– (2nd and 3rd instars)

Gasterophilus nasalis– (3rd instars)

Tapeworms:

Anoplocephala perfoliata – (adults)

One administration of the recommended dose rate of QUEST PLUS Gel also suppresses strongyle egg production through 84 days.

STRATEGIC PROTECTION PROGRAMS

Consult your veterinarian for assistance in the diagnosis, treatment, and control of parasitism. For best control of parasites, all horses and ponies should be included in a strategic treatment program, with particular attention given to high performance animals. In foals, initial treatment is recommended at 6 months of age, after which they should be included in a recurrent treatment program. Because QUEST PLUS Gel provides eff ective control of the mucosal stages of small strongyles (encysted cyathostomes) and tapeworms, it is useful in reducing the frequency of treatment required for successful strategic equine parasite control. A veterinarian can assist in preparing the best program for your needs.

QUEST PLUS Gel when used at the recommended dose rate suppresses strongyle egg production through 84 days following a single oral administration. This residual strongyle control reduces pasture contamination and provides a period of protection from reinfection for horses and ponies maintained on the same pasture.

MODE OF ACTION

QUEST PLUS Gel contains two active pharmaceutical ingredients, moxidectin and praziquantel. Moxidectin acts by interfering with chloride channel-mediated neurotransmission in the parasite. This results in paralysis and elimination of the parasite. Moxidectin is safe for use in horses and ponies because it does not have the same injurious eff ect on the mammalian nervous system. Praziquantel increases the tapeworm’s membrane permeability to calcium and other cations causing severe contraction and paralysis of the tapeworm’s muscles.

This spastic paralysis results in the inability of tapeworms to attach to the host’s intestinal wall.
Detached tapeworms are either destroyed by the host’s immune defense system or passed in the feces.

ADMINISTRATION AND DOSAGE

QUEST PLUS Gel is specially formulated as a palatable gel which is easily administered to horses and ponies. QUEST PLUS Gel is packaged in ready-to-use SURE-DIAL® syringes. The syringe is calibrated in 50-pound increments, up to 1500 pounds. This enables the administration of the recommended dose level by choosing a setting consistent with the animal’s weight.

Do not underdose. Ensure each animal receives a complete dose based on a current body weight. Underdosing may result in ineff ective treatment, and encourage the development of parasite resistance.

HOW TO SET THE DOSE

Since the dose is based on the weight of the animal, you need to use a scale or weight tape to find each animal’s weight before treating with QUEST PLUS Gel. Once the weight is known, set the dose for each horse or pony as follows.
1. Hold the syringe with the capped end pointing to the left and so that you can see the
weight measurements and tick marks (small black lines). Each tick mark relates to 50 lb
of body weight.
2. Turn the white dial ring until the left side of the ring lines up with the weight of the animal.

HOW TO GIVE QUEST PLUS GEL TO A HORSE OR PONY

1. Make sure there is no feed in the animal’s mouth.
2. Remove the cap from the end of the syringe. Save the cap for reuse.
3. Place the tip of the syringe inside the animal’s mouth at the space between the teeth.
4. Gently push the plunger until it stops, depositing the gel on the back of the tongue.
5. Remove the syringe from the animal’s mouth and raise the animal’s head slightly to make
sure it swallows the gel.
6. Replace the syringe cap.

TREATING A SECOND HORSE OR PONY WITH THE SAME SYRINGE

If the first animal you treat weighs less than 1500 lb, there will be gel left in the syringe. You can use this gel to treat other horses or ponies. To set the next dose, add the weight of the animal you want to treat to the dose setting already on the syringe. For example, if the syringe was first used to treat a 250 lb animal, the white dial ring is set on 250 lb. To treat a 500 lb animal next, move the white dial ring to the 750 lb marking (250+500=750). You need more than one syringe to treat horses weighing more than 1500 lb.

ANIMAL SAFETY

QUEST PLUS Gel can be safely administered at the recommended dose to horses and ponies of all breeds at least 6 months of age and older. Transient ataxia, incoordination, lethargy, depression and droopy lips and eyelids may be seen when very young or debilitated animals are treated. In these instances, supportive care may be advisable. QUEST PLUS Gel is safe for use in breeding, pregnant, and lactating mares. In a reproductive safety study, 10 mares received QUEST PLUS Gel at three times the recommended dosage, and 10 mares received tap water (control). Mares were dosed at least once a month from breeding through 30 days post-foaling, with increased frequency (every 2 weeks) around breeding. Nine out of 10 QUEST PLUS Gel treated mares became pregnant, and gave birth to live foals. Ten control mares became pregnant, and 8 out of the 10 mares gave birth to live foals.

One QUEST PLUS Gel treated mare had episodes of depression, decreased appetite, and diarrhea shortly after receiving 5 of the 17 (29%) doses. The same mare had one episode of colic shortly after one administration of QUEST PLUS Gel. This mare’s colic, depression, decreased appetite, and diarrhea all resolved without treatment. Another QUEST PLUS Gel treated mare had an abnormal reproductive cycle (prolonged time to ovulation) following foal heat (at least 39 days). This mare became pregnant on the fi rst breeding and gave birth to a female foal that was normal at birth; however, the foal developed an enlarged clitoris by Day 30 post-foaling. To report adverse drug reactions or to obtain a copy of the Safety Data Sheet (SDS) call 1-888-963-8471.

ENVIRONMENTAL SAFETY

Care should be taken to avoid the release of significant volumes of this product into either ground or free-running water since moxidectin may be injurious to aquatic life. SURE-DIAL® syringes and their contents should be disposed of in an approved landfill or by incineration.

PRECAUTIONS

QUEST PLUS Gel has been formulated specifically for use in horses and ponies only.

Reproductive safety studies on breeding stallions have not been conducted.

This product should not be used in other animal species as severe adverse reactions, including fatalities in dogs, may result.

WARNINGS

Extreme caution should be used when administering the product to foals, young and miniature horses, as overdosage may result in serious adverse reactions. Do not use in sick, debilitated, or underweight animals. Do not use in horses intended for human consumption.

HUMAN WARNINGS

Not for use in humans. Keep this and all drugs out of the reach of children. Do not ingest. If swallowed, induce vomiting. Wash hands and contaminated skin with soap and water. If accidental contact with eyes occurs, flush repeatedly with water. If irritation or any other symptom attributable to exposure to this product persists, consult your physician.

OTHER WARNINGS

Parasite resistance may develop to any dewormer, and has been reported for most classes of dewormers. Treatment with a dewormer used in conjunction with parasite management practices appropriate to the geographic area and the animal(s) to be treated may slow the development of parasite resistance. Fecal examinations or other diagnostic tests and parasite management history should be used to determine if the product is appropriate for the herd prior to the use of any dewormer. Following the use of any dewormer, effectiveness of treatment should be monitored (for example, with the use of a fecal egg count reduction test or another appropriate method). A decrease in a drug’s effectiveness over time as calculated by fecal egg count reduction tests may indicate the development of resistance to the dewormer administered. Your parasite management plan should be adjusted accordingly based on regular monitoring.

HOW SUPPLIED

QUEST PLUS Gel is available in one syringe applicator size.
Each SURE-DIAL® syringe contains 0.5 oz (14.0 g) of QUEST PLUS Gel which is suffi cient to treat a single horse weighing up to 1500 lb, or two or more lighter animals with a combined body weight of up to 1500 lb.

0.5 oz (14.0 g) syringe - 20 mg moxidectin and 125 mg praziquantel per mL

Store at or below 77°F (25°C). Avoid freezing. If frozen, thaw completely before use. Store partially used syringes with the cap tightly secured.

zoetis

Distributed by:
Zoetis Inc.
Kalamazoo, MI 49007

Revised: May 2019

40027574